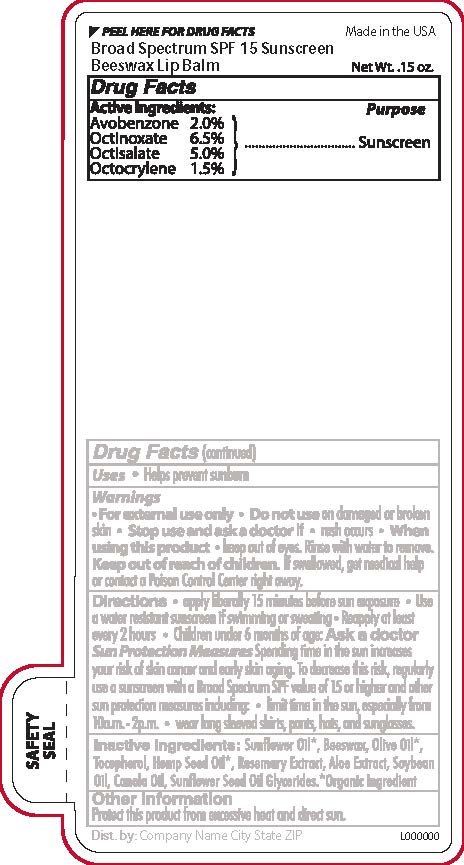 DRUG LABEL: Beeswax SPF 15 Broad Spectrum Lip Balm
NDC: 65692-0591 | Form: STICK
Manufacturer: Raining Rose, Inc
Category: otc | Type: HUMAN OTC DRUG LABEL
Date: 20250210

ACTIVE INGREDIENTS: OCTISALATE 0.21 g/4.25 g; AVOBENZONE 0.09 g/4.25 g; OCTOCRYLENE 0.06 g/4.25 g; OCTINOXATE 0.28 g/4.25 g
INACTIVE INGREDIENTS: SUNFLOWER OIL MONO/DIGLYCERIDES; CANOLA OIL; SOYBEAN OIL; WHITE WAX; SUNFLOWER OIL; TOCOPHEROL; ROSEMARY; OLIVE OIL; CANNABIS SATIVA SEED OIL; ALOE VERA LEAF

BS SPF 15 Beeswax Lip Balm

Active Ingredients

Avobenzone 2.0%

Octinoxate 6.5%

Octisalate 5.0%

Octocrylene 1.5%

Purpose

Sunscreen

Warnings

For external use only

Do not use

on damaged or broken skin.

Stop Use and ask a doctor if

Rash Occurs

When Using this Product

Keep out of eyes. Rinse well with water to remove.

Keep out of reach of children

If swallowed, get medical help or contact a Poison Control Center right away.

Directions

Apply liberally 15 minutes before sun exposure

Use a water resistant sunscreen if swimming or sweating

Reapply at least every 2 hours
Children under 6 months of age: Ask a doctor

Inactive ingredients:

Sunflower Oil*, Beeswax, Olive Oil*, Tocopherol, Hemp Seed Oil*, Rosemary Extract, Aloe Extract, Soybean Oil, Canola Oil, Sunflower Seed Oil Glycerides. * Organic

DOSAGE AND ADMINISTRATION

Apply liberally 15 mintues before sun exposure

INDICATIONS AND USAGE

Helps prevent sunburn